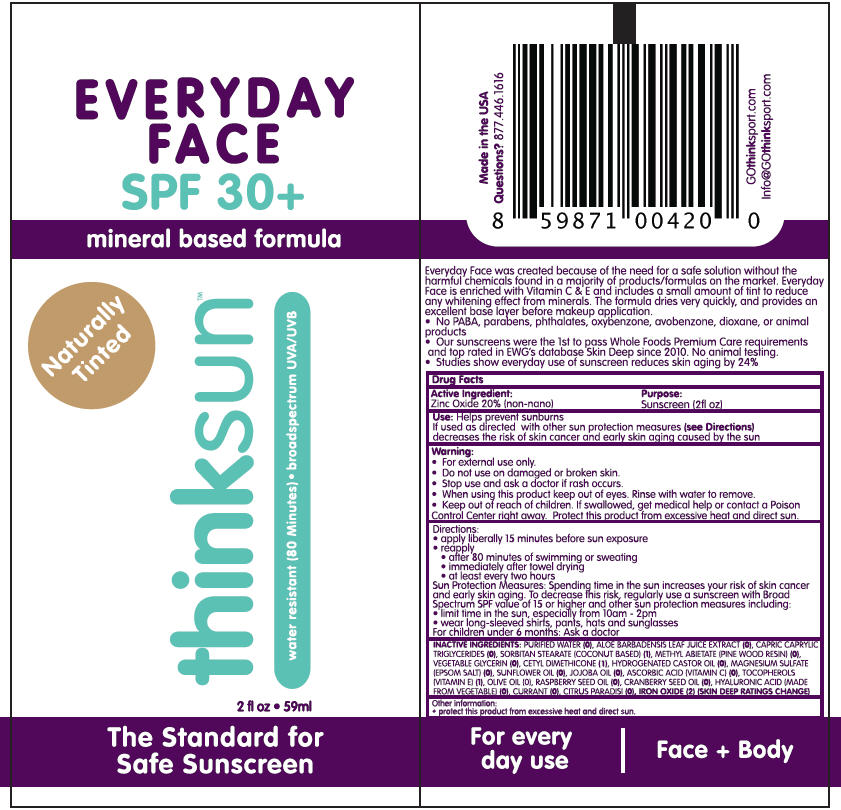 DRUG LABEL: Thinksport Thinksun 
NDC: 60781-1010 | Form: LOTION
Manufacturer: thinkOperations,LLC
Category: otc | Type: HUMAN OTC DRUG LABEL
Date: 20190325

ACTIVE INGREDIENTS: zinc oxide 200 mg/1 mL
INACTIVE INGREDIENTS: WATER; ALOE VERA LEAF; TRICAPRIN; SORBITAN MONOSTEARATE; PINUS MUGO BARK; GLYCERIN; CETYL DIMETHICONE 25; HYDROGENATED CASTOR OIL; MAGNESIUM SULFATE, UNSPECIFIED FORM; SUNFLOWER OIL; JOJOBA OIL; ASCORBIC ACID; TOCOPHEROL; OLIVE OIL; RASPBERRY SEED OIL; CRANBERRY SEED OIL; HYALURONIC ACID; BLACK CURRANT JUICE; FERRIC OXIDE RED

Thinksport Thinksun™
Sunscreen SPF 30

Drug Facts

Active Ingredient

Zinc Oxide 20% (non-nano)

Purpose

Sunscreen (2fl oz)

Use

Helps prevent sunburns

If used as directed with other sun protection measures (see Directions) decreases the risk of skin cancer and early skin aging caused by the sun

Warnings

- For external use only.

- Do not use on damaged or broken skin.

- Stop use and ask a doctor if rash occurs.

- When using this product keep out of eyes. Rinse with water to remove.

- Keep out of reach of children. If swallowed, get medical help or contact a Poison Control Center right away. Protect this product from excessive heat and direct sun.

Directions

- apply liberally 15 minutes before sun exposure
- reapply
  - after 80 minutes of swimming or sweating
  - immediately after towel drying
  - at least every two hours

Sun Protection Measures

Spending time in the sun increases your risk of skin cancer and early skin aging. To decrease this risk, regularly use a sunscreen with Broad Spectrum SPF value of 15 or higher and other sun protection measures including:

- limit time in the sun, especially from 10am - 2pm
- wear long-sleeved shirts, pants, hats and sunglasses

For children under 6 months: Ask a doctor

INACTIVE INGREDIENTS

PURIFIED WATER (0), ALOE BARBADENSIS LEAVE JUICE EXTRACT (0), CAPRIC CAPRYLIC TRIGLYCERIDES (0), SORBITAN STEARATE (COCONUT BASED) (1), METHYL ABIETATE (PINE WOOD RESIN) (0), VEGETABLE GLYCERIN (0), CETYL DIMETHICONE (1), HYDROGENATED CASTOR OIL (0), MAGNESIUM SULFATE (EPSOM SALT) (0), SUNFLOWER OIL (0), JOJOBA OIL (0), ASCORBIC ACID (VITAMIN C) (0), TOCOPHEROLS (VITAMIN E) (1), OLIVE OIL (0), RASPBERRY SEED OIL (0), CRANBERRY SEED OIL (0), HYALURONIC ACID (MADE FROM VEGETABLE) (0), CURRANT (0), CITRUS PARADISI (0), IRON OXIDE (2) (SKIN DEEP RATINGS CHANGE)

Other information

- protect this product from excessive heat and direct sun.

Questions?

877.446.1616

PRINCIPAL DISPLAY PANEL - 59 ml Tube Label

EVERYDAY
FACE
SPF 30+

mineral based formula

Naturally
Tinted

thinksun™

water resistant (80 Minutes) • broadspectrum UVA/UVB

2 fl oz • 59ml

The Standard for
Safe Sunscreen